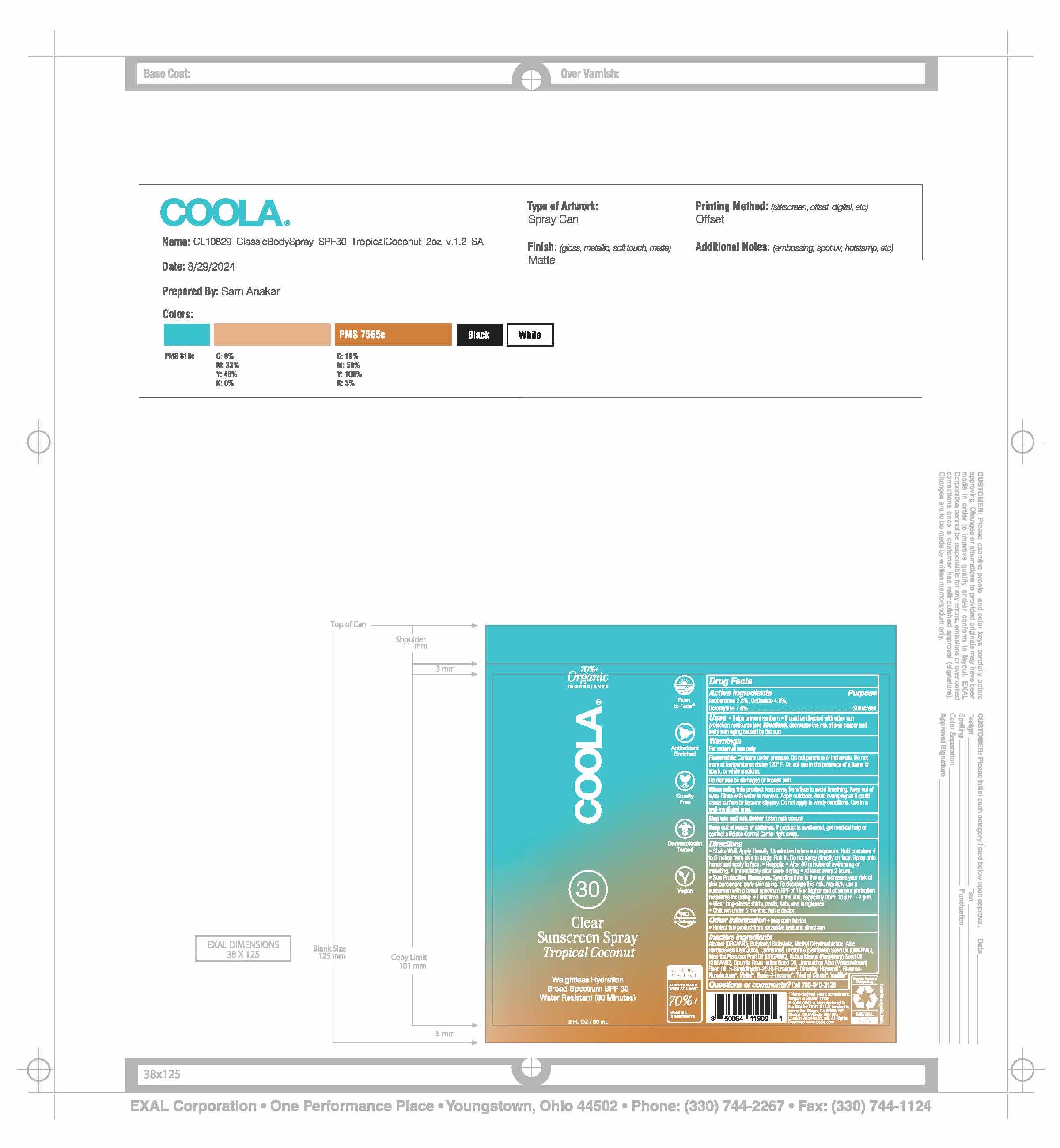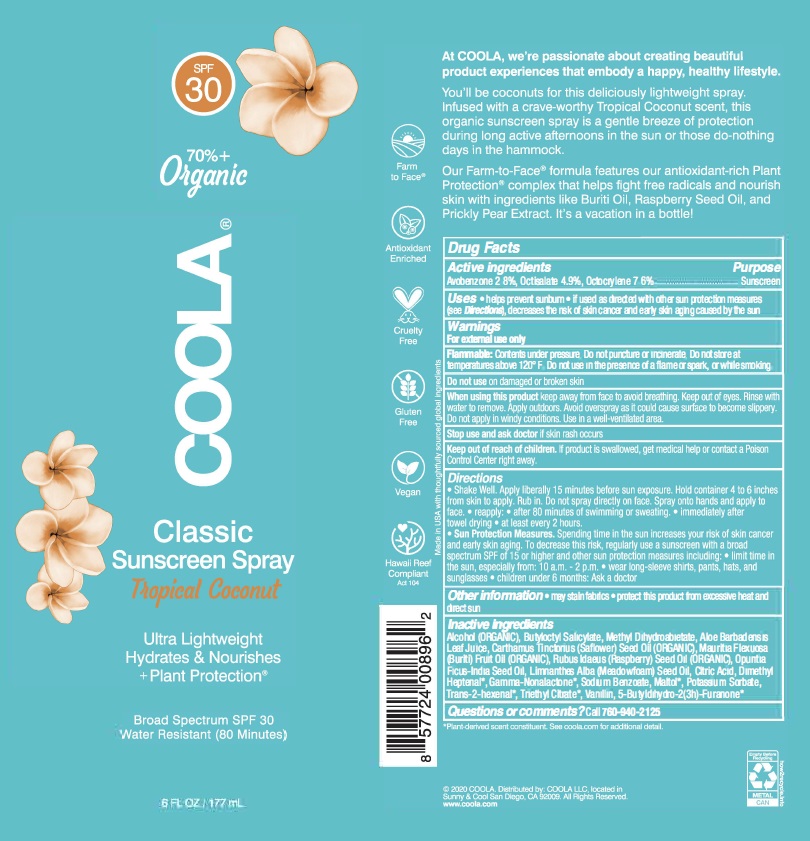 DRUG LABEL: COOLA Classic Body SPF 30 Tropical Coconut
NDC: 79753-062 | Form: SPRAY
Manufacturer: COOLA, LLC
Category: otc | Type: HUMAN OTC DRUG LABEL
Date: 20250225

ACTIVE INGREDIENTS: AVOBENZONE 2.8 g/100 mL; OCTISALATE 4.9 g/100 mL; OCTOCRYLENE 7.6 g/100 mL
INACTIVE INGREDIENTS: MALTOL; TRIETHYL CITRATE; 2-HEXENAL, (2E)-; .GAMMA.-OCTALACTONE; .GAMMA.-NONALACTONE; 2,6-DIMETHYL-5-HEPTENAL; VANILLIN; ALOE VERA LEAF; ALCOHOL; BUTYLOCTYL SALICYLATE; POTASSIUM SORBATE; SAFFLOWER OIL; OPUNTIA FICUS-INDICA SEED OIL; CITRIC ACID MONOHYDRATE; RASPBERRY SEED OIL; MEADOWFOAM SEED OIL; METHYL DIHYDROABIETATE; MAURITIA FLEXUOSA FRUIT OIL; SODIUM BENZOATE

Coola Classic Body Spray SPF 30 - Tropical Coconut

ACTIVE INGREDIENT

Avobenzone - 2.8%
Octisalate - 4.9%
Octocrylene - 7.6%

PURPOSE

Sunscreen

Uses

- Helps prevent sunburn
- If used as directed with other sun protection measures (see Directions), decreases the nsk of skin cancer and early skin aging caused by the sun

WARNINGS

- For external use only
- Flammable: Contents under pressure. Do not puncture or incinerat. Do not store at temperatures above 120 F. Do not use in the presence of a flame or spark, or while smoking.
- Do not use on damaged or broken skin.
- When using this product keep away from face to avoid breathing. Keep out of eyes. Rinse with water to remove. Apply outdoors. Avoid overspray as it could cause surface to become slippery. Do not apply in windy conditions. Use in a well-ventilated area.
- Stop use and ask a doctor if rash occurs.

Keep out of reach of children. If product is swallowed, get medical help or contact a Poison Control Center right away.

Directions

- Shake Well
- Apply liberally 15 minutes before sun exposure.
- Hold container 4 to 6 inches from skin to apply.
- Rub in. Do not spray directly on face.
- Spray onto hands and apply to face.
- Reapply: After 80 minutes of swimming or sweating. Immediately after towel drying. At least every 2 hours.
- Sun Protection Measures. Spending time in the sun increases your risk of skin cancer and early skin aging. To decrease this risk, regularly use a sunscreen with a Broad Spectrum SPF value of 15 or higher and other sun protection measures including: • Limit time in the sun especially from 10 a.m. – 2 p.m. • Wear long-sleeved shirts, pants, hats, and sunglasses.
- Children under six months: Ask a doctor.

INACTIVE INGREDIENT

Alcohol (ORGANIC), Butyloctyl Salicylate, Methyl Dihydroabietate, Aloe Barbadensis Leaf Juice, Carthamus Tinctorius (Safflower) Seed Oil (ORGANIC), Mauritia Flexuosa (Buriti) Fruit Oil (ORGANIC), Rubus Idaeus (Raspberry) Seed Oil (ORGANIC), Opuntia Ficus-Indica Seed Oil, Limnanthes Alba (Meadowfoam) Seed Oil, Citric Acid, Dimethyl Heptenal, Gamma-Nonalactone, Sodium Benzoate, Maltol, Potassium Sorbate, Trans-2-hexenal, Triethyl Citrate, Vanillin, 5-Butyldihydro-2(3H)-Furanone

OTHER SAFETY INFORMATION

- May stain fabrics
- Protect this product from excessive heat and direct sun

QUESTIONS

Call 760-940-2125